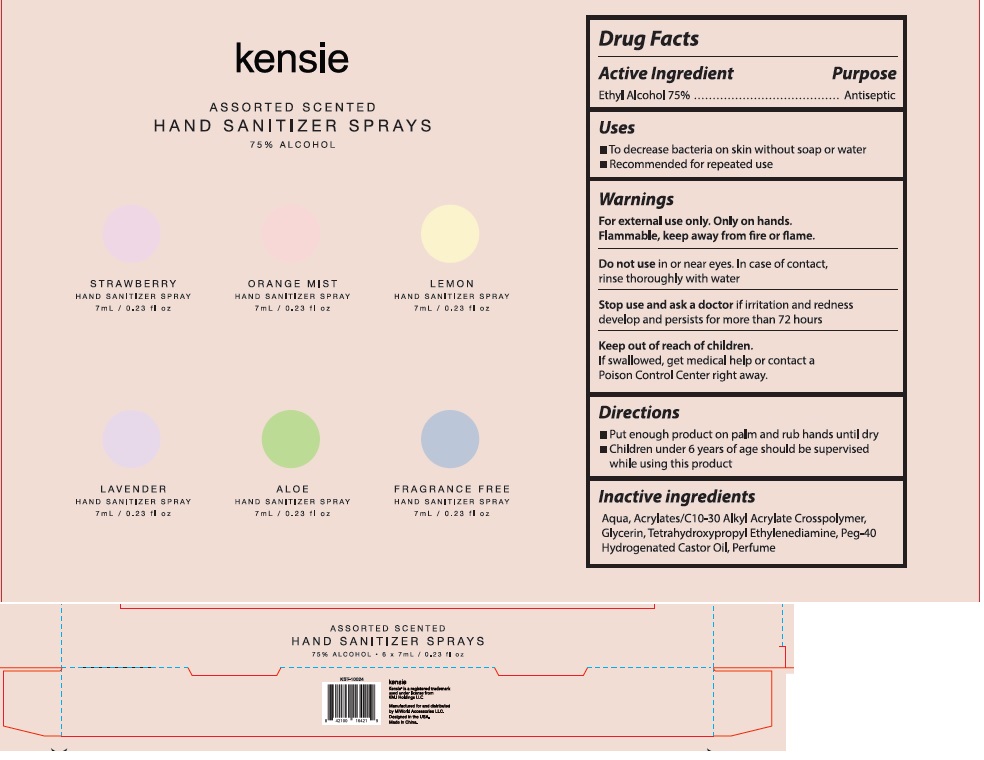 DRUG LABEL: Assorted Scented Hand Sanitizers
NDC: 74274-016 | Form: SPRAY
Manufacturer: Huizhou Bliss Commodity Co., Ltd
Category: otc | Type: HUMAN OTC DRUG LABEL
Date: 20200522

ACTIVE INGREDIENTS: ALCOHOL 75 mL/100 mL
INACTIVE INGREDIENTS: WATER; CARBOMER COPOLYMER TYPE A; GLYCERIN; POLYOXYL 40 HYDROGENATED CASTOR OIL; EDETOL

Active ingredient

Ethyl Alcohol 75%

Purpose

Antiseptic

Use

- To decrease bacteria on skin without soap or water
- Recommended for repeated use

KEEP OUT OF REACH OF CHILDREN

if swallowed, get medical help or contact a Poison Control Center right away.

warnings:

Flamable, keep away from fire and flame.

For external use only hands.

Do not use in or near eye. In case of contact with, rinse thoroughly with water.

Stop use and ask a doctor

If irritation and redness develops.and persists for more than 72 hours

Directions

- Put enough product on palm and rub hands until dry
- Children under 6 year of age should be supervised while using this product

Inactive ingredients

Aqua, Acrylates/C10-30 Alkyl Acrylate Crosspolymer, Glycerin, Tetrahydroypropyl Ethylenediamine, Peg-40 Hydrogenated Cator Oil, Perfume